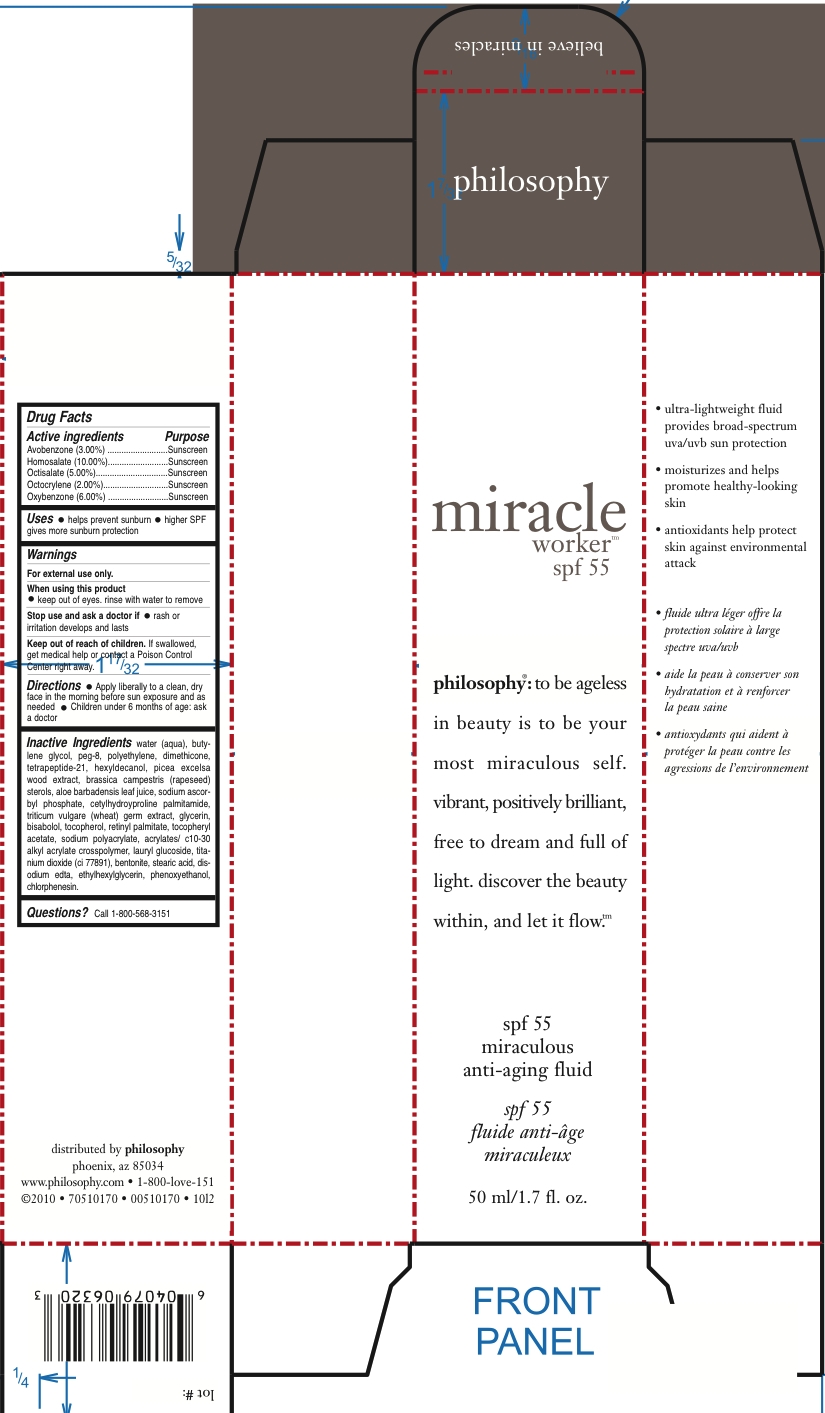 DRUG LABEL: Miracle Worker SPF 55
NDC: 50184-6500 | Form: CREAM
Manufacturer: Philosophy, Inc
Category: otc | Type: HUMAN OTC DRUG LABEL
Date: 20110124

ACTIVE INGREDIENTS: AVOBENZONE 1.5 mL/50 mL; HOMOSALATE 5 mL/50 mL; OCTISALATE 2.5 mL/50 mL; OCTOCRYLENE 1 mL/50 mL; OXYBENZONE 3 mL/50 mL
INACTIVE INGREDIENTS: WATER; BUTYLENE GLYCOL; POLYETHYLENE GLYCOL 400; POLYETHYLENE GLYCOL; DIMETHICONE; HEXYLDECANOL; BRASSICA RAPA VAR. RAPA; ALOE VERA LEAF; SODIUM ASCORBYL PHOSPHATE; WHEAT GERM; GLYCERIN; LEVOMENOL; ALPHA-TOCOPHEROL; VITAMIN A PALMITATE; .ALPHA.-TOCOPHEROL ACETATE, D-; CARBOMER INTERPOLYMER TYPE A (55000 CPS); LAURYL GLUCOSIDE; TITANIUM DIOXIDE; BENTONITE; STEARIC ACID; EDETATE DISODIUM; ETHYLHEXYLGLYCERIN; PHENOXYETHANOL; CHLORPHENESIN; TETRAPEPTIDE-21; PICEA ABIES WOOD; CETYLHYDROXYPROLINE PALMITAMIDE; SODIUM POLYACRYLATE (8000 MW)

DRUG FACTS

ACTIVE INGREDIENT

AVOBENZONE (3.00%)........SUNSCREEN

HOMOSALATE (10.00%)......SUNSCREEN

OCTISALATE (5.00%)...........SUNSCREEN

OCTOCRYLENE (2.00%).......SUNSCREEN

OXYBENZONE (6.00%).........SUNSCREEN

PURPOSE

HELPS PREVENT SUNBURN

HIGHER SPF GIVES MORE PROTECTION

WARNINGS

FOR EXTERNAL USE ONLY

WHEN USING

KEEP OUT OF EYES. RINSE WITH WATER TO REMOVE.

STOP USE AND ASK A DOCTOR IF RASH OR IRRITATION DEVELOPS AND LASTS.

KEEP OUT OF REACH OF CHILDREN. IF SWALLOWED GET MEDICAL HELP OR CONTACT A POISON CONTROL CENTER RIGHT AWAY.

INDICATIONS AND USAGE

APPLY LIBERALLY TO CLEAN, DRY FACE IN THE MORNING BEFORE SUN EXPOSURE AND AS NEEDED. CHILDREN UNDER 6 MONTHS OF AGE: ASK A DOCTOR.

INACTIVE INGREDIENT

WATER (AQUA), BUTYLENE GLYCOL, PEG-8, POLYETHYLENE, DIMETHICONE, TETRAPEPTIDE-21, HEXYLDECANOL, PICEA EXCELSA WOOD EXTRACT, BRASSICA CAMPESTRIS (RAPESEED) STEROLS, ALOE BARBADENSIS LEAF JUICE, SODIUM ASCORBYL PHOSPHATE, CETYLHYDROXYPROLINE PALMITAMIDE, TRITICUM VULGARE (WHEAT) GERM EXTRACT, GLYCERIN, BISABOLOL, TOCOPHEROL, RETINYL PALMITATE, TOCOPHERYL ACETATE, SODIUM POLYACRYLATE, ACRYLATES/C10-30 ALKYL ACRYLATE CROSSPOLYMER, LAURYL GLUCOSIDE, TITANIUM DIOXIDE, BENTONITE, STEARIC ACID, DISODIUM EDTA, ETHYLHEXYLGLYCERIN, PHENOXYETHANOL, CHLORPHENESIN.

PACKAGE LABEL

Enter section text here